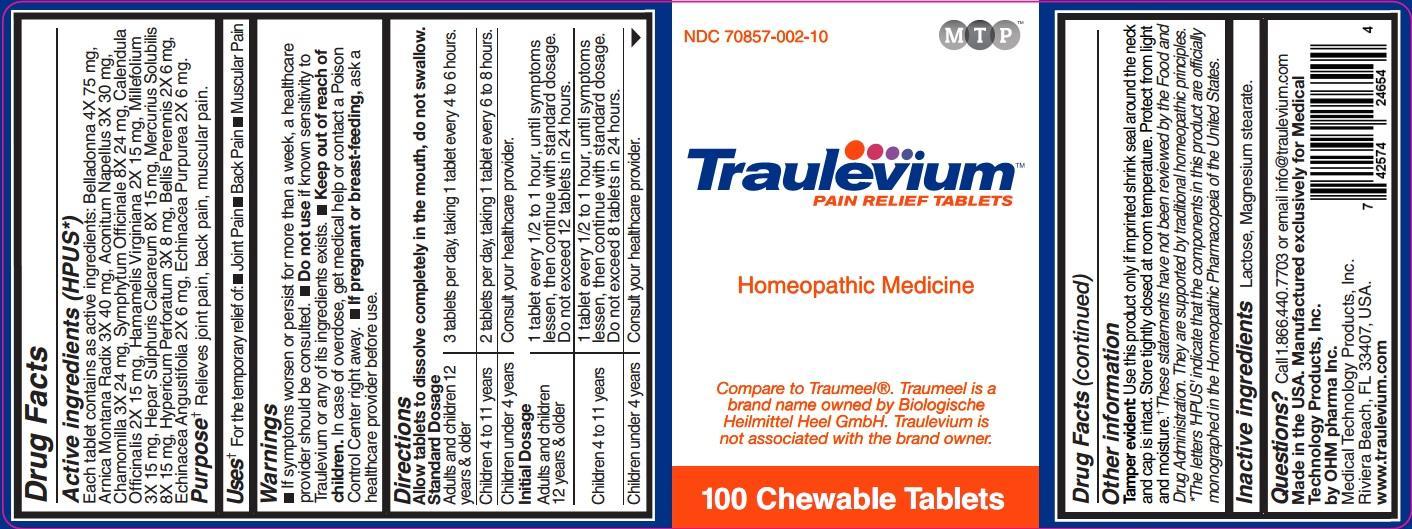 DRUG LABEL: Traulevium
NDC: 70857-002 | Form: TABLET, CHEWABLE
Manufacturer: Medical Technology Products, Inc.
Category: homeopathic | Type: HUMAN OTC DRUG LABEL
Date: 20211229

ACTIVE INGREDIENTS: ATROPA BELLADONNA 4 [hp_X]/1 1; ARNICA MONTANA 3 [hp_X]/1 1; ACONITUM NAPELLUS 3 [hp_X]/1 1; MATRICARIA RECUTITA 3 [hp_X]/1 1; COMFREY ROOT 8 [hp_X]/1 1; CALENDULA OFFICINALIS FLOWERING TOP 2 [hp_X]/1 1; HAMAMELIS VIRGINIANA ROOT BARK/STEM BARK 2 [hp_X]/1 1; ACHILLEA MILLEFOLIUM 3 [hp_X]/1 1; CALCIUM SULFIDE 8 [hp_X]/1 1; MERCURIUS SOLUBILIS 8 [hp_X]/1 1; HYPERICUM PERFORATUM 3 [hp_X]/1 1; BELLIS PERENNIS 2 [hp_X]/1 1; ECHINACEA ANGUSTIFOLIA 2 [hp_X]/1 1; ECHINACEA PURPUREA 2 [hp_X]/1 1
INACTIVE INGREDIENTS: LACTOSE; MAGNESIUM STEARATE

Traulevium PAIN RELIEF TABLETS

Active ingredients (HPUS*)

Each tablet contains as active ingredients: Belladonna 4X 75 mg, Arnica Montana Radix 3X 40 mg, Aconitum Napellus 3X 30 mg, Chamomilla 3X 24 mg, Symphytum Officinale 8X 24 mg, Calendula Officinalis 2X 15 mg, Hamamelis Virginiana 2X 15 mg, Millefolium 3X 15 mg, Hepar Sulphuris Calcareum 8X 15 mg, Mercurius Solubilis 8X 15 mg, Hypericum Perforatum 3X 8 mg, Bellis Perennis 2X 6 mg, Echinacea Angustifolia 2X 6 mg, Echinacea Purpurea 2X 6 mg.

Purpose** Relieves joint pain, back pain, muscular pain.

INDICATIONS AND USAGE

Uses** For the temporary relief of:

- Joint Pain
- Back Pain
- Muscular Pain

Warnings

- If symptoms worsen or persist for more than a week, a healthcare provider should be consulted.
- Do not use if known sensitivity to Traulevium or any of its ingredients exists.
- Keep out of the reach of children. In case of overdose, get medical help or contact a Poison Control Center right away.
- If pregnant or breast-feeding, ask a healthcare provider before use.

Keep out of reach of children.

Directions

Allow tablets to dissolve completely in the mouth, do not swallow.

Standard Dosage
Adults and children 12 years & older | 3 tablets per day, taking 1 tablet every 4 to 6 hours.
Children 4 to 11 years | 2 tablets per day, taking 1 tablet every 6 to 8 hours.
Children under 4 years | Consult your healthcare provider.
Initial Dosage
Adults and children 12 years & older | 1 tablet every 1/2 to 1 hour, until symptoms lessen, then continue with standard dosage. Do not exceed 12 tablets in 24 hours.
Children 4 to 11 years | 1 tablet every 1/2 to 1 hour, until symptoms lessen, then continue with standard dosage. Do not exceed 8 tablets in 24 hours.
Children under 4 years | Consult your healthcare provider.

Other information

Tamper evident: Use this product only if imprinted shrink seal around the neck and cap is intact. Store tightly closed at room temperature. Protect from light and moisture.

**These statements have not been reviewed by the Food and Drug Administration. They are supported by traditional homeopathic principles.

*The letters 'HPUS' indicate that the components in this product are officially monographed in the Homeopathic Pharmacopeia of the United States.

Inactive ingredients Lactose, Magnesium stearate.

QUESTIONS

Questions? Call 1.866.440.7703 or email info@traulevium.com

Made in the USA. Manufactured exclusively for Medical Technology Products, Inc. by OHM pharma Inc.

Medical Technology Products, Inc.

Riviera Beach, FL 33407, USA.

www.traulevium.com

PACKAGE LABEL

NDC 70857-002-10

MTP

Traulevium™

PAIN RELIEF TABLETS

Homeopathic Medicine

Compare to Traumeel®. Traumeel is a brand name owned by Biologische Heilmittel Heel GmbH. Traulevium is not associated with the brand owner.

100 Chewable Tablets